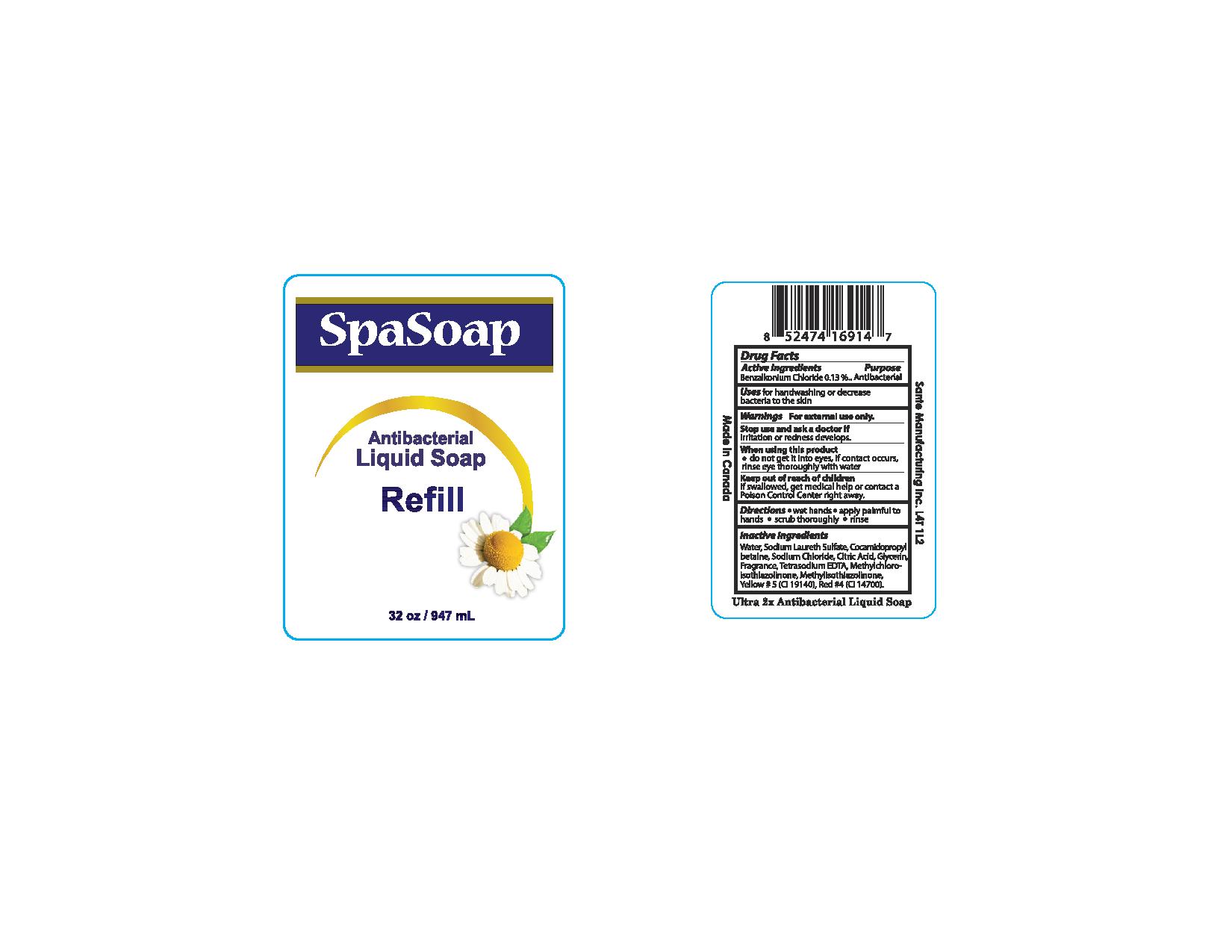 DRUG LABEL: Antibacterial
NDC: 71020-003 | Form: LIQUID
Manufacturer: Sante Manufcaturing Inc
Category: otc | Type: HUMAN OTC DRUG LABEL
Date: 20250107

ACTIVE INGREDIENTS: BENZALKONIUM CHLORIDE 1.3 mg/1 mL
INACTIVE INGREDIENTS: SODIUM LAURETH SULFATE; SODIUM CHLORIDE; GLYCERIN; DITETRACYCLINE TETRASODIUM EDETATE; WATER; COCAMIDOPROPYL BETAINE; ANHYDROUS CITRIC ACID; METHYLCHLOROISOTHIAZOLINONE; METHYLISOTHIAZOLINONE; FD&C YELLOW NO. 5; FD&C RED NO. 4

ACTIVE INGREDIENT

Benzalkonium Chloride - 0.13%

Purpose - Antibacterial

INDICATIONS AND USAGE

Uses for handwashing or decrease bacteria to the skin

WARNINGS

Warning For external use only

Stop use and ask a doctor if irritation or redness develops

When using the product

- Do not get into eyes. If contact occurs rinse eye thoroughly with water

Keep out of reach of children

If swallowed, get medical help or contact a Poison Control Center right away

DOSAGE AND ADMINISTRATION

Direction

- Wet hands
- apply palmful to hands
- scrub thoroughly
- rinse

INACTIVE INGREDIENT

Water, Sodium Laureth Sulfate, Cocamidopropyl Betaine, Sodium Chloride, Citric Acid, Glycerin, Fragrance, Tetrasodium EDTA, Methylchloroisothiazolinone, Methylisothiazolinone, Yellow #5 (Cl 19140), Red #4 (Cl 14700)

PACKAGE LABEL

Spa Soap Antibacterial Liquid Soap